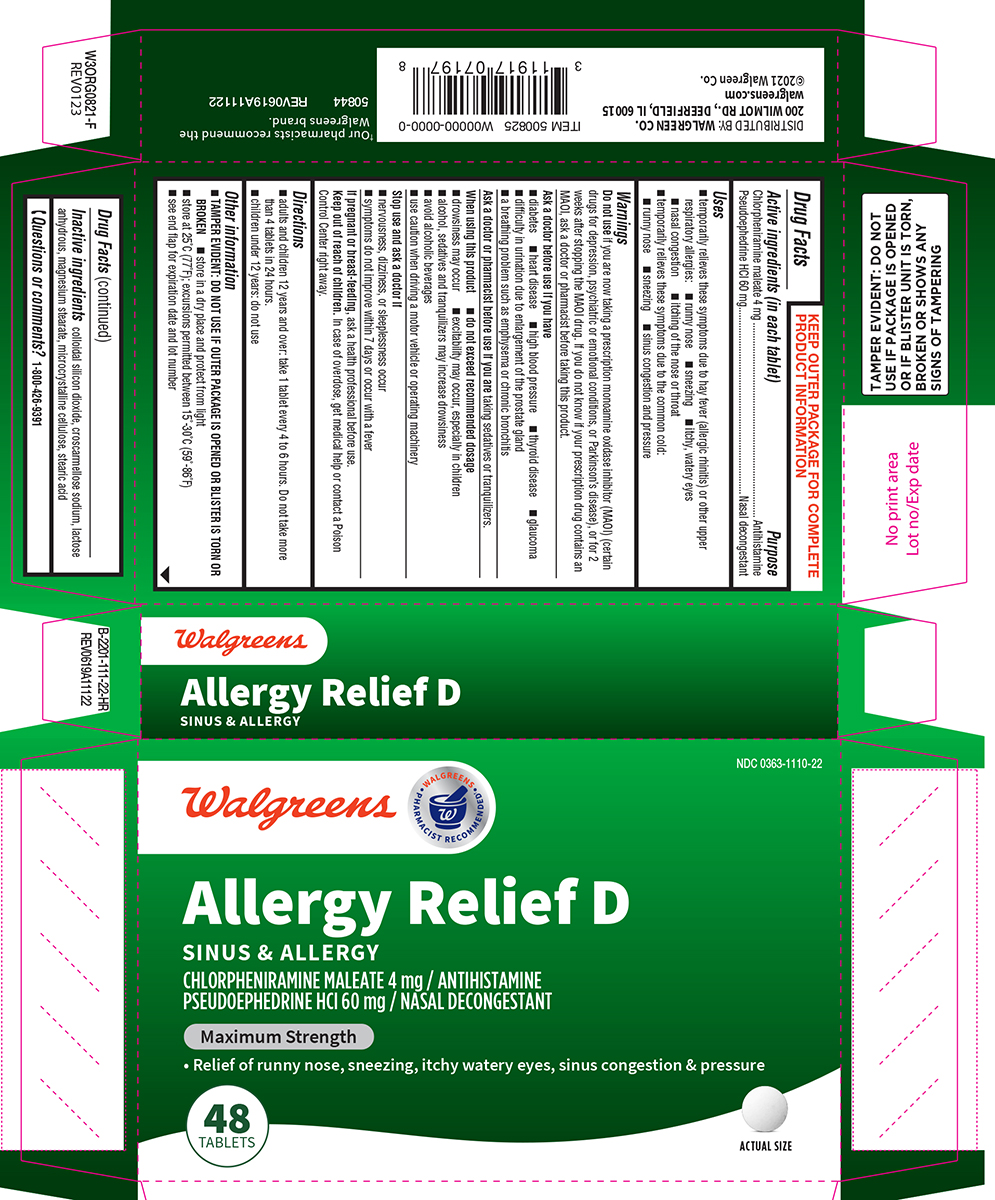 DRUG LABEL: Allergy Relief D
NDC: 0363-1110 | Form: TABLET
Manufacturer: Walgreen Company
Category: otc | Type: HUMAN OTC DRUG LABEL
Date: 20250718

ACTIVE INGREDIENTS: CHLORPHENIRAMINE MALEATE 4 mg/1 1; PSEUDOEPHEDRINE HYDROCHLORIDE 60 mg/1 1
INACTIVE INGREDIENTS: SILICON DIOXIDE; CROSCARMELLOSE SODIUM; ANHYDROUS LACTOSE; MAGNESIUM STEARATE; MICROCRYSTALLINE CELLULOSE; STEARIC ACID

Walgreens 44-111-Allergy Relief

Active ingredients (in each tablet)

Chlorpheniramine maleate 4 mg
Pseudoephedrine HCl 60 mg

Purpose

Antihistamine
Nasal decongestant

Uses

- temporarily relieves these symptoms due to hay fever (allergic rhinitis) or other upper respiratory allergies:
  - runny nose
  - sneezing
  - itchy, watery eyes
  - nasal congestion
  - itching of the nose or throat
- temporarily relieves these symptoms due to the common cold:
  - runny nose
  - sneezing
  - sinus congestion and pressure

Warnings

Do not use

if you are now taking a prescription monoamine oxidase inhibitor (MAOI) (certain drugs for depression, psychiatric or emotional conditions, or Parkinson’s disease), or for 2 weeks after stopping the MAOI drug. If you do not know if your prescription drug contains an MAOI, ask a doctor or pharmacist before taking this product.

Ask a doctor before use if you have

- diabetes
- heart disease
- high blood pressure
- thyroid disease
- glaucoma
- difficulty in urination due to enlargement of the prostate gland
- a breathing problem such as emphysema or chronic bronchitis

Ask a doctor or pharmacist before use if you are

taking sedatives or tranquilizers.

When using this product

- do not exceed recommended dosage
- drowsiness may occur
- excitability may occur, especially in children
- alcohol, sedatives and tranquilizers may increase drowsiness
- avoid alcoholic beverages
- use caution when driving a motor vehicle or operating machinery

Stop use and ask a doctor if

- nervousness, dizziness, or sleeplessness occur
- symptoms do not improve within 7 days or occur with a fever

If pregnant or breast-feeding,

ask a health professional before use.

Keep out of reach of children.

In case of overdose, get medical help or contact a Poison Control Center right away.

Directions

- adults and children 12 years and over: take 1 tablet every 4 to 6 hours. Do not take more than 4 tablets in 24 hours.
- children under 12 years: do not use

Other information

- TAMPER EVIDENT: DO NOT USE IF OUTER PACKAGE IS OPENED OR BLISTER IS TORN OR BROKEN
- store in a dry place and protect from light
- store at 25°C (77°F); excursions permitted between 15°-30°C (59°-86°F)
- see end flap for expiration date and lot number

Inactive ingredients

colloidal silicon dioxide, croscarmellose sodium, lactose anhydrous, magnesium stearate, microcrystalline cellulose, stearic acid

Questions or comments?

1-800-426-9391

Principal display panel

NDC 0363-1110-22

Walgreens

• WALGREENS •
PHARMACIST RECOMMENDED†

Allergy Relief D
SINUS & ALLERGY
CHLORPHENIRAMINE MALEATE 4 mg / ANTIHISTAMINE
PSEUDOEPHEDRINE HCI 60 mg / NASAL DECONGESTANT

Maximum Strength

• Relief of runny nose, sneezing, itchy, watery eyes, sinus congestion & pressure

48
TABLETS

ACTUAL SIZE

TAMPER EVIDENT: DO NOT
USE IF PACKAGE IS OPENED
OR IF BLISTER UNIT IS TORN,
BROKEN OR SHOWS ANY
SIGNS OF TAMPERING

†Our pharmacists recommend the Walgreens brand.

50844 REV0619A11122

DISTRIBUTED BY: WALGREEN CO.
200 WILMOT RD., DEERFIELD, IL 60015
walgreens.com
©2021 Walgreen Co.

Walgreens 44-111